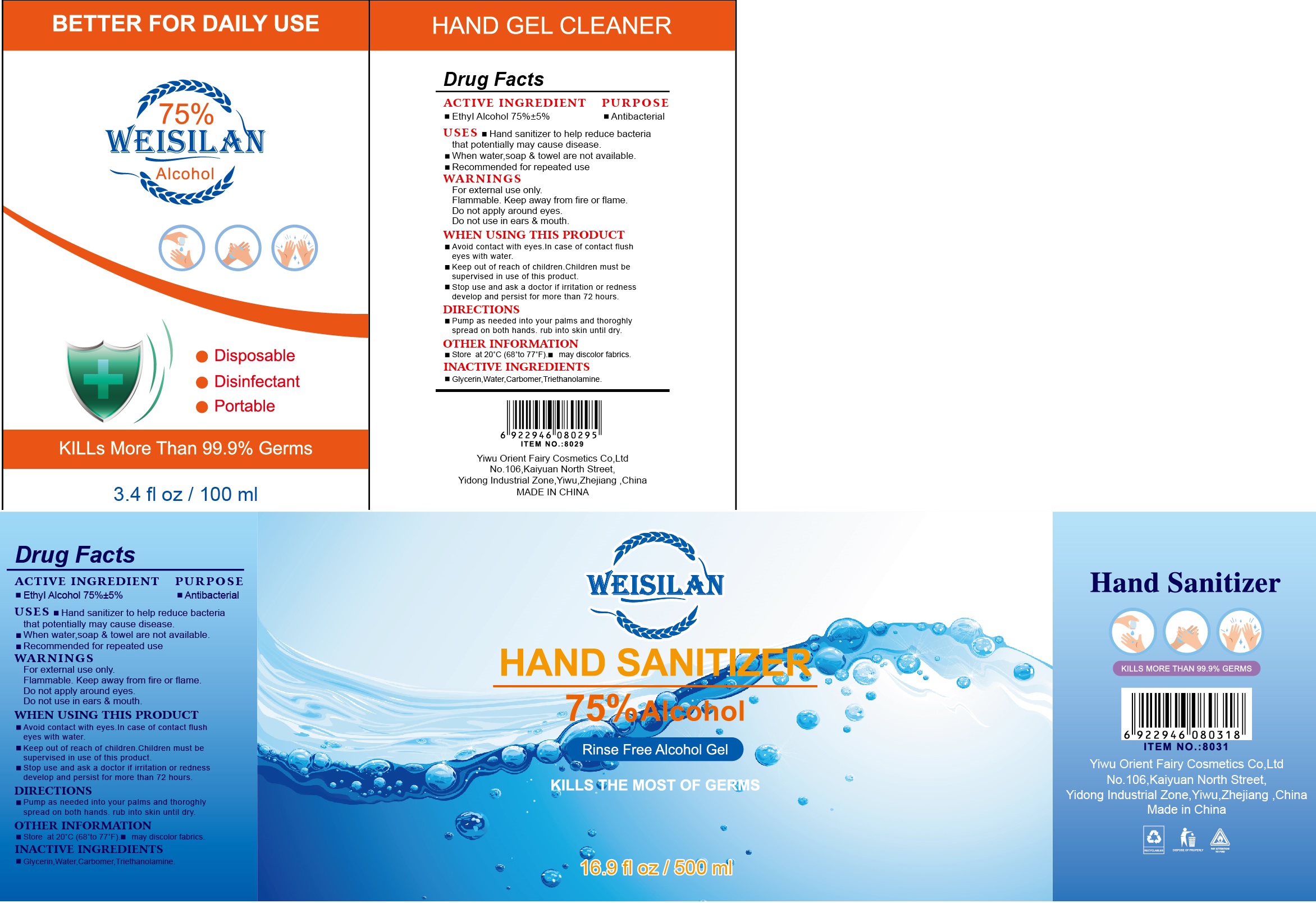 DRUG LABEL: Weisilan Hand Sanitizer
NDC: 78057-008 | Form: GEL
Manufacturer: YIWU ORIENT FAIRY COSMETICS CO.,LTD.
Category: otc | Type: HUMAN OTC DRUG LABEL
Date: 20200519

ACTIVE INGREDIENTS: ALCOHOL 75 mL/100 mL
INACTIVE INGREDIENTS: WATER; GLYCERIN; TROLAMINE; CARBOMER 940

Active ingredient

Ethyl Alcohol 75% (V/V) ±5%

Purpose

Antibacterial

Use

- Hand sanitizer to help reduce bacteria that potentially may cause diseasse.
- When water, soap and towel are not available.
- Recommended for repatd use.

Warnings

For external use only.

Flammable, Keep away from fire or flame

Do not apply around eyes.

Do not use in ears and mouth

When using this product

Avoid contact with eyes, ears. In case of contact, flush eyes with water.

Stop use and ask a doctor if

irritation or redness develop and persist for more than 72 hours.

Keep out of reach of children.

Children must be supervised in use of this product.

Directions

- Pump as needed into your palms and thoroughly spread on both hands. Rub into skin until dry.

Inactive ingredients

Glycerin, Water, Carbomer, Triethanolamine.

Other information

- Store between 20 ℃ (68-77 ℉).
- may discolor fabrics.